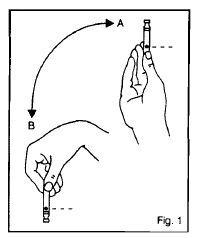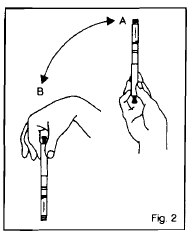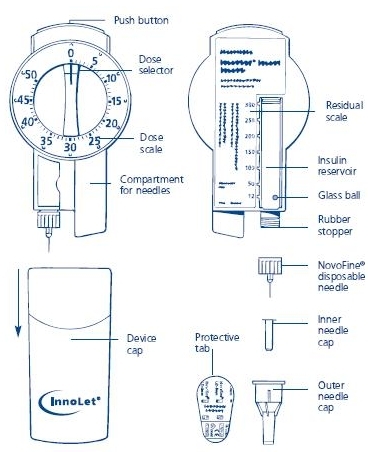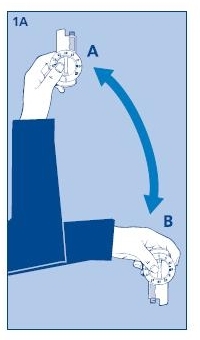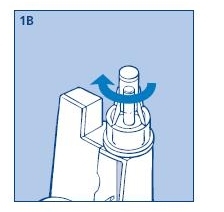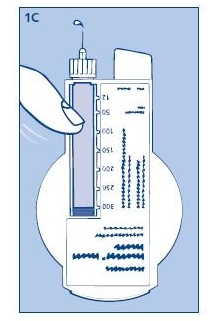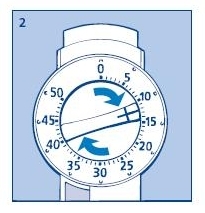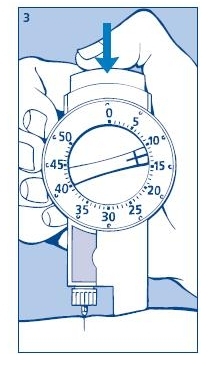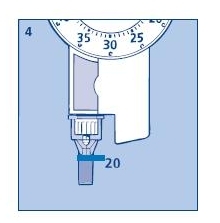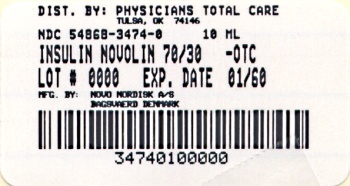 DRUG LABEL: Novolin
NDC: 54868-3474 | Form: INJECTION, SUSPENSION
Manufacturer: Physicians Total Care, Inc.
Category: otc | Type: HUMAN OTC DRUG LABEL
Date: 20120111

ACTIVE INGREDIENTS: INSULIN HUMAN 100 [USP'U]/1 mL
INACTIVE INGREDIENTS: GLYCERIN; METACRESOL; PHENOL; PROTAMINE SULFATE; SODIUM PHOSPHATE, DIBASIC, DIHYDRATE; ZINC CHLORIDE; HYDROCHLORIC ACID; SODIUM HYDROXIDE; WATER

Novolin® 70/30, 70% NPH, Human Insulin Isophane Suspension and 30% Regular, Human Insulin Injection (recombinant DNA origin)

PATIENT PACKAGE INSERT

Patient Information for Novolin® 70/30

NOVOLIN® 70/30 (NO-voe-lin)

70% NPH, Human Insulin Isophane Suspension and

30% Regular, Human Insulin Injection

(recombinant DNA origin) 100 units/mL

PURPOSE

Important:

Know your insulin. Do not change the type of insulin you use unless told to do so by your healthcare provider. The amount of insulin you take as well as the best time for you to take your insulin may need to change if you take a different type of insulin.

Make sure that you know the type and strength of insulin that is prescribed for you.

Read the Patient Information leaflet that comes with Novolin 70/30 before you start taking it and each time you get a refill. There may be new information. This leaflet does not take the place of talking with your healthcare provider about your diabetes or your treatment. Make sure you know how to manage your diabetes. Ask your healthcare provider if you have any questions about managing your diabetes.

What is Novolin 70/30?

Novolin 70/30 is a man-made insulin (recombinant DNA origin) which is a mixture of 70% NPH, Human Insulin Isophane Suspension and 30% Regular, Human Insulin Injection that is structurally identical to the insulin produced by the human pancreas that is used to control high blood sugar in patients with diabetes mellitus.

DO NOT USE

Who should not use Novolin 70/30?

Do not take Novolin 70/30 if:

- Your blood sugar is too low (hypoglycemia).
- You are allergic to anything in Novolin 70/30. See the end of this leaflet for a complete list of ingredients in Novolin 70/30. Check with your healthcare provider if you are not sure.

ASK YOUR DOCTOR

Tell your healthcare provider:

- about all of your medical conditions. Medical conditions can affect your insulin needs and your dose of Novolin 70/30.
- if you are pregnant or breastfeeding. You and your healthcare provider should talk about the best way to manage your diabetes while you are pregnant or breastfeeding. Novolin 70/30 has not been studied in pregnant or nursing women.
- about all of the medicines you take, including prescription and non-prescription medicines, vitamins and herbal supplements. Many medicines can affect your blood sugar levels and your insulin needs. Your Novolin 70/30 dose may need to change if you take other medicines.

Know the medicines you take. Keep a list of your medicines with you to show all your healthcare providers when you get a new medicine.

DOSAGE AND ADMINISTRATION

How should I take Novolin 70/30?

Only use Novolin 70/30 if it appears cloudy or milky. There may be air bubbles. This is normal. If the precipitate (the white deposit at the bottom of the vial) has become lumpy or granular in appearance or has formed a deposit of solid particles on the wall of the vial, do not use it, and call Novo Nordisk at 1-800-727-6500. This insulin should not be used if the liquid in the vial remains clear after the vial has been gently rotated.

Novolin 70/30 comes in:

- 10 mL vials (small bottles) for use with syringe

INDICATIONS AND USAGE

Read the instructions for use that come with your Novolin 70/30 product. Talk to your healthcare provider if you have any questions. Your healthcare provider should show you how to inject Novolin 70/30 before you start taking it. Follow your healthcare provider’s instructions to make changes to your insulin dose.

- Take Novolin 70/30 exactly as prescribed.
- Novolin 70/30 is an intermediate-acting insulin. The effects of Novolin 70/30 start working ½ hour after injection.
- The greatest blood sugar lowering effect is between 2 and 12 hours after the injection. This blood sugar lowering may last up to 24 hours.
- While using Novolin 70/30, any change of insulin should be made cautiously and only under medical supervision. Doses of oral anti-diabetic medicines may also need to change, if your insulin is changed.
- Do not mix Novolin 70/30 with any insulins.
- Inject Novolin 70/30 into the skin of your stomach area, upper arms, buttocks or upper legs. Novolin 70/30 may affect your blood sugar levels sooner if you inject it into the skin of your stomach area. Never inject Novolin 70/30 into a vein or into a muscle.
- Change (rotate) your injection site within the chosen area (for example, stomach or upper arm) with each dose. Do not inject into the same spot for each injection.
- If you take too much Novolin 70/30, your blood sugar may fall low (hypoglycemia). You can treat mild low blood sugar (hypoglycemia) by drinking or eating something sugary right away (fruit juice, sugar candies, or glucose tablets). It is important to treat low blood sugar (hypoglycemia) right away because it could get worse and you could pass out (become unconscious). If you pass out, you will need help from another person or emergency medical services right away, and will need treatment with a glucagon injection or treatment at a hospital. See “What are the possible side effects of Novolin 70/30?” for more information on low blood sugar (hypoglycemia).
- If you forget to take your dose of Novolin 70/30, your blood sugar may go too high (hyperglycemia). If high blood sugar (hyperglycemia) is not treated it can lead to diabetic ketoacidosis, which can lead to serious problems, like loss of consciousness (passing out), coma or even death. Follow your healthcare provider’s instructions for treating high blood sugar (hyperglycemia), and talk to your healthcare provider if high blood sugar is a problem for you. Severe or continuing high blood sugar (hyperglycemia) requires prompt evaluation and treatment by your healthcare provider. Know your symptoms of high blood sugar (hyperglycemia) and diabetic ketoacidosis which may include:
-
  - increased thirst
  - frequent urination and dehydration
  - confusion or drowsiness
  - loss of appetite
  - fruity smell on breath
  - high amounts of sugar and ketones in your urine
  - nausea, vomiting (throwing up) or stomach pain
  - a hard time breathing
- Check your blood sugar levels. Ask your healthcare provider how often you should check your blood sugar levels for hypoglycemia (too low blood sugar) and hyperglycemia (too high blood sugar).

Your insulin dosage may need to change because of:

- illness
- stress
- other medicines you take

- change in diet
- change in physical activity or exercise
- surgery

See the end of this patient information for instructions about preparing and giving the injection.

What should I avoid while using Novolin 70/30?

- Alcohol. Alcohol, including beer and wine, may affect your blood sugar when you take Novolin 70/30.
- Driving and operating machinery. You may have difficulty concentrating or reacting if you have low blood sugar (hypoglycemia). Be careful when you drive a car or operate machinery. Ask your healthcare provider if it is alright to drive if you often have:
  - low blood sugar
  - decreased or no warning signs of low blood sugar

ADVERSE EFFECTS

What are the possible side effects of Novolin 70/30?

Low blood sugar (hypoglycemia). Symptoms of hypoglycemia (low blood sugar) may include:

- sweating
- dizziness or lightheadedness
- shakiness
- hunger
- fast heart beat
- tingling of lips and tongue

- trouble concentrating or confusion
- blurred vision
- slurred speech
- anxiety, irritability or mood changes
- headache

Severe low blood sugar (hypoglycemia) can cause unconsciousness (passing out), seizures, and death. Know your symptoms of low blood sugar. Follow your healthcare provider’s instructions for treating low blood sugar. Talk to your healthcare provider if low blood sugar is a problem for you.

- Serious allergic reaction (whole body reaction). Get medical help right away if you develop a rash over your whole body, have trouble breathing, a fast heartbeat, or sweating.
- Reactions at the injection site (local allergic reaction). You may get redness, swelling, and itching at the injection site. If you keep having skin reactions, or they are serious, talk to your healthcare provider. You may need to stop using Novolin 70/30 and use a different insulin. Do not inject insulin into skin that is red, swollen, or itchy.
- Skin thickens or pits at the injection site (lipodystrophy). Change (rotate) where you inject your insulin to help prevent these skin changes from happening. Do not inject insulin into this type of skin.
- Swelling of your hands and feet
- Vision changes
- Low potassium in your blood (hypokalemia)

These are not all of the possible side effects from Novolin 70/30. Ask your healthcare provider or pharmacist for more information.

Call your doctor for medical advice about side effects. You may report side effects to FDA at 1-800-FDA-1088.

STORAGE AND HANDLING

How should I store Novolin 70/30?

All Unopened Novolin 70/30:

- Keep all unopened Novolin 70/30 in the refrigerator between 36° to 46°F (2° to 8°C).
- Do not freeze. Do not use Novolin 70/30 if it has been frozen.
- If refrigeration is not possible, the unopened vial may be kept at room temperature for up to 6 weeks (42 days), as long as it is kept at or below 77°F (25°C).
- Keep unopened Novolin 70/30 in the carton to protect from light.

Novolin 70/30 in use:

Vials

- Keep at room temperature below 77°F (25°C) for up to 6 weeks (42 days).
- Keep vials away from direct heat or light.
- Throw away an opened vial after 6 weeks (42 days) of use, even if there is insulin left in the vial.
- Unopened vials can be used until the expiration date on the Novolin 70/30 label, if the medicine has been stored in a refrigerator.

General advice about Novolin 70/30

Novolin 70/30 is used for the treatment of diabetes only. Medicines are sometimes prescribed for conditions that are not mentioned in the patient leaflet. Do not use Novolin 70/30 for a condition for which it was not prescribed. Do not give Novolin 70/30 to other people, even if they have the same symptoms you have. It may harm them.

This leaflet summarizes the most important information about Novolin 70/30. If you would like more information about Novolin 70/30 or diabetes, talk with your healthcare provider. For more information, call 1-800-727-6500 or visit www.novonordisk-us.com.

Helpful information for people with diabetes is published by the American Diabetes Association, 1701 N Beauregard Street, Alexandria, VA 22311 and on www.diabetes.org.

ACTIVE INGREDIENTS

Novolin 70/30 ingredients include:

- 70% NPH, Human Insulin Isophane Suspension and 30% Regular, Human Insulin Injection (recombinant DNA origin)

INACTIVE INGREDIENTS

Novolin 70/30 ingredients include:

- Zinc chloride
- Sodium hydroxide
- Phenol
- Disodium phosphate dihydrate

- Metacresol
- Glycerol
- Hydrochloric acid
- Protamine sulfate
- Water for injections

All Novolin 70/30 vials are latex-free.

Date of issue: May 14, 2010

Version: 5

Novolin® and Novo Nordisk® are trademarks of Novo Nordisk A/S.

© 2005-2010 Novo Nordisk A/S

Manufactured by:

Novo Nordisk A/S

DK-2880 Bagsvaerd, Denmark

For information about Novolin 70/30 contact:

Novo Nordisk Inc.

100 College Road West

Princeton, New Jersey 08540

Patient Instructions for Use

Novolin® 70/30 10 mL vial (100 Units/mL, U-100)

Before starting, gather all of the supplies that you will need to use for preparing and giving your insulin injection.

Never re-use syringes and needles.

How should I use the Novolin 70/30 vial?

1. Check to make sure that you have the correct type of insulin.
2. Look at the vial and the insulin. The insulin should be a cloudy or milky suspension. The tamper-resistant cap should be in place before the first use. If the cap had been removed before your first use of the vial, or if the precipitate (the white deposit at the bottom of the vial) has become lumpy or granular in appearance or has formed a deposit of solid particles on the wall of the vial, do not use it, and call Novo Nordisk at 1-800-727-6500.
3. Wash your hands with soap and water. If you clean your injection site with an alcohol swab, let the injection site dry before you inject. Talk with your healthcare provider about how to rotate injection sites and how to give an injection.
4. If you are using a new vial, pull off the tamper-resistant cap. Wipe the rubber stopper with an alcohol swab.
5. Roll the vial gently 10 times in your hands to mix it. This procedure should be carried out with the vial in a horizontal position. The rolling procedure must be repeated until the suspension appears uniformly white and cloudy. Shaking right before the dose is drawn into the syringe may cause bubbles or froth, which could cause you to draw up the wrong dose of insulin.
6. Pull back the plunger on the syringe until the black tip reaches the marking for the number of units you will inject.
7. Push the needle through the rubber stopper of the vial, and push the plunger all the way in to force air into the vial.
8. Turn the vial and syringe upside down and slowly pull the plunger back to a few units beyond the correct dose.
9. If there are any air bubbles, tap the syringe gently with your finger to raise the air bubbles to the top. Then slowly push the plunger to the marking for your correct dose. This process should move any air bubbles present in the syringe back into the vial.
10. Check to make sure you have the right dose of Novolin 70/30 in the syringe.
11. Pull the syringe with needle out of the vial’s rubber stopper.
12. Your doctor should tell you if you need to pinch the skin before inserting the needle. This can vary from patient to patient so it is important to ask your doctor if you did not receive instructions on pinching the skin. Insert the needle into the skin. Press the plunger of the syringe to inject the insulin. When you are finished injecting the insulin, pull the needle out of your skin. You may see a drop of Novolin 70/30 at the needle tip. This is normal and has no effect on the dose you just received. If you see blood after you take the needle out of your skin, press the injection site lightly with a piece of gauze or an alcohol wipe. Do not rub the area.
13. After your injection, do not recap the needle. Place used syringes, needles and used insulin vials in a disposable puncture-resistant sharps container, or some type of hard plastic or metal container with a screw on cap such as a detergent bottle or coffee can.
14. Ask your healthcare provider about the right way to throw away used syringes and needles. There may be state or local laws about the right way to throw away used syringes and needles. Do not throw away used needles and syringes in household trash or recycle.

Information for the patient

Novolin®70/30 PenFill®

70% NPH, Human Insulin Isophane Suspension and

30% Regular, Human Insulin Injection

(recombinant DNA origin)

3 mL Disposable Cartridge

(300 units per cartridge)

100 units/mL (U-100)

Please read this leaflet carefully before using this product.

Please note the special directions under PREPARING THE INJECTION.

Novolin® 70/30 PenFill® 3 mL is designed for use with Novo Nordisk® 3 mL PenFill cartridge compatible insulin delivery devices, with or without the addition of a NovoPen® 3 PenMate®, and NovoFine® disposable needles.

PenFill® cartridge is for single-person use only. See IMPORTANT NOTES section.

WARNING

ANY CHANGE OF INSULIN SHOULD BE MADE CAUTIOUSLY AND ONLY UNDER MEDICAL SUPERVISION. CHANGES IN PURITY, STRENGTH, BRAND (MANUFACTURER), TYPE (REGULAR, NPH, LENTE®, ETC.), SPECIES (BEEF, PORK, BEEF-PORK, HUMAN), AND/OR METHOD OF MANUFACTURE (RECOMBINANT DNA VERSUS ANIMAL-SOURCE INSULIN) MAY RESULT IN THE NEED FOR A CHANGE IN DOSAGE.

SPECIAL CARE SHOULD BE TAKEN WHEN THE TRANSFER IS FROM A STANDARD BEEF OR MIXED SPECIES INSULIN TO A PURIFIED PORK OR HUMAN INSULIN. IF A DOSAGE ADJUSTMENT IS NEEDED, IT WILL USUALLY BECOME APPARENT EITHER IN THE FIRST FEW DAYS OR OVER A PERIOD OF SEVERAL WEEKS. ANY CHANGE IN TREATMENT SHOULD BE CAREFULLY MONITORED.

PLEASE READ THE SECTIONS “INSULIN REACTION AND SHOCK” AND “DIABETIC KETOACIDOSIS AND COMA” FOR SYMPTOMS OF HYPOGLYCEMIA (LOW BLOOD GLUCOSE) AND HYPERGLYCEMIA (HIGH BLOOD GLUCOSE).

INSULIN USE IN DIABETES

Your physician has explained that you have diabetes and that your treatment involves injections of insulin or insulin therapy combined with an oral antidiabetic medicine. Insulin is normally produced by the pancreas, a gland that lies behind the stomach. Without insulin, glucose (a simple sugar made from digested food) is trapped in the bloodstream and cannot enter the cells of the body. Some patients who don’t make enough of their own insulin, or who cannot use the insulin they do make properly, must take insulin by injection in order to control their blood glucose levels.

Each case of diabetes is different and requires direct and continued medical supervision. Your physician has told you the type, strength and amount of insulin you should use and the time(s) at which you should inject it, and has also discussed with you a diet and exercise schedule. You should contact your physician if you experience any difficulties or if you have questions.

TYPES OF INSULINS

Standard and purified animal insulins as well as human insulins are available. Standard and purified insulins differ in their degree of purification and content of noninsulin material. Standard and purified insulins also vary in species source; they may be of beef, pork, or mixed beef and pork origin. Human insulin is identical in structure to the insulin produced by the human pancreas, and thus differs from animal insulins. Insulins vary in time of action; see PRODUCT DESCRIPTION for additional information. Your physician has prescribed the insulin that is right for you; be sure you have purchased the correct insulin and check it carefully before you use it.

PRODUCT DESCRIPTION

This package contains five (5) Novolin® 70/30 PenFill® 3 mL cartridges. Novolin 70/30 is a mixture of 70% NPH, Human Insulin Isophane Suspension and 30% Regular, Human Insulin Injection (recombinant DNA origin). The concentration of this product is 100 units of insulin per milliliter. It is a cloudy or milky suspension of human insulin with protamine and zinc. The insulin substance (the cloudy material) settles at the bottom of the cartridge, therefore, the cartridge must be rotated up and down as described under PREPARING THE INJECTION so that the contents are uniformly mixed before a dose is given. Novolin 70/30 has an intermediate duration of action. The effect of Novolin 70/30 begins approximately ½ hour after injection. The effect is maximal between 2 and approximately 12 hours. The full duration of action may last up to 24 hours after injection.

The time course of action of any insulin may vary considerably in different individuals, or at different times in the same individual. Because of this variation, the time periods listed here should be considered as general guidance only.

This human insulin (recombinant DNA origin) is structurally identical to the insulin produced by the human pancreas. This human insulin is produced by recombinant DNA technology utilizing Saccharomyces cerevisiae (bakers’ yeast) as the production organism.

INSULIN DELIVERY SYSTEMS

These Novolin 70/30 PenFill 3 mL cartridges are designed for use with Novo Nordisk® 3 mL PenFill cartridge compatible insulin delivery devices, with or without the addition of a NovoPen® 3 PenMate®, and NovoFine® disposable needles.

STORAGE

Insulin should be stored in a cold (36° - 46°F [2° - 8°C]) place, preferably in a refrigerator, but not in the freezer. Do not let it freeze. Keep Novolin 70/30 PenFill cartridges in the carton so that they will stay clean and protected from light. The Novolin 70/30 PenFill cartridge that you are currently using should not be refrigerated but should be kept as cool as possible (below 86°F [30°C]) and away from direct heat and light. Unrefrigerated Novolin 70/30 PenFill cartridges must be discarded 10 days after the first use, even if they still contain Novolin 70/30 insulin.

Never use PenFill cartridges after the expiration date which is printed on the label and carton.

Never use any Novolin 70/30 PenFill cartridge if the precipitate (the white deposit) has become lumpy or granular in appearance or has formed a deposit of solid particles on the wall of the cartridge. This insulin should not be used if the liquid in the cartridge remains clear after it has been mixed.

IMPORTANT

Failure to follow the antiseptic measures listed below may lead to infections at the injection site.

– Disposable needles are for single use; they should be used only once and destroyed.

– Clean your hands and the injection site with soap and water or with alcohol.

– Wipe the rubber stopper on the insulin cartridge with an alcohol swab.

PREPARING THE INJECTION

Never place a single-use disposable needle on your insulin delivery device until you are ready to give an injection, and remove it immediately after the injection. If the needle is not removed, some liquid may be expelled from the cartridge causing a change in the insulin concentration (strength).

The cloudy material in an insulin suspension will settle to the bottom of the cartridge, so the contents must be mixed before injection. These Novolin PenFill cartridges contain a glass ball to aid mixing.

Figure 1
Figure 2

When using a new cartridge, turn the cartridge up and down between positions A and B – See Figure 1. Do this at least 10 times until the liquid appears uniformly white and cloudy. Assemble your insulin delivery device following the directions in your instruction manual. For subsequent injections when a cartridge is already in the device, turn the device up and down between positions A and B - See Figure 2. Do this at least 10 times until the liquid appears uniformly white and cloudy. Follow the directions in your insulin delivery device instruction manual.

Note: Never initiate a new injection unless there is sufficient insulin in the cartridge to ensure proper mixing (the glass ball needs adequate room for movement to mix the suspension).

PenFill cartridges may contain a small amount of air bubbles. To prevent an injection of air and to make certain that a full dose of insulin is injected, an air shot must be done before each injection. Directions for performing an air shot are provided in your insulin delivery device instruction manual.

GIVING THE INJECTION

1. The following areas are suitable for subcutaneous insulin injection: thighs, upper arms, buttocks, abdomen. Do not change areas without consulting your physician. The actual point of injection should be changed each time; injection sites should be about an inch apart.
2. The injection site should be clean and dry. Pinch up skin area to be injected and hold it firmly.
3. Hold the device like a pencil and push the needle quickly and firmly into the pinched-up area.
4. Release the skin and push the push button all the way in to inject insulin beneath the skin. After the injection, the needle should remain under the skin for at least 6 seconds. Keep the push button fully depressed until the needle is withdrawn from the skin. This will ensure that the full dose has been injected.
5. Do not inject into a muscle unless your physician has advised it. You should never inject insulin into a vein. Follow the directions for use of your insulin delivery device.
6. Remove the needle. If slight bleeding occurs, press lightly with a dry cotton swab for a few seconds - do not rub.

Note: Use the injection technique recommended by your physician.

USAGE IN PREGNANCY

It is particularly important to maintain good control of your diabetes during pregnancy and special attention must be paid to your diet, exercise and insulin regimens. If you are pregnant or nursing a baby, consult your physician or nurse educator.

INSULIN REACTION AND SHOCK

Insulin reaction (hypoglycemia) occurs when the blood glucose falls very low. This can happen if you take too much insulin, miss or delay a meal, exercise more than usual, or work too hard without eating, or become ill (especially with vomiting or fever). Hypoglycemia can also happen if you combine insulin therapy and other medications that lower blood glucose, such as oral antidiabetic agents or other prescription and over-the-counter drugs. The first symptoms of an insulin reaction usually come on suddenly. They may include a cold sweat, fatigue, nervousness or shakiness, rapid heartbeat, or nausea. Personality change or confusion may also occur. If you drink or eat something right away (a glass of milk or orange juice, or several sugar candies), you can often stop the progression of symptoms. If symptoms persist, call your physician - an insulin reaction can lead to unconsciousness. If a reaction results in loss of consciousness, emergency medical care should be obtained immediately. If you have had repeated reactions or if an insulin reaction has led to a loss of consciousness, contact your physician. Severe hypoglycemia can result in temporary or permanent impairment of brain function and death.

In certain cases, the nature and intensity of the warning symptoms of hypoglycemia may change. A few patients have reported that after being transferred to human insulin, the early warning symptoms of hypoglycemia were less pronounced than they had been with animal-source insulin.

DIABETIC KETOACIDOSIS AND COMA

Diabetic ketoacidosis may develop if your body has too little insulin. The most common causes are acute illness or infection or failure to take enough insulin by injection. If you are ill, you should check your urine for ketones. The symptoms of diabetic ketoacidosis usually come on gradually, over a period of hours or days, and include a drowsy feeling, flushed face, thirst and loss of appetite. Notify your physician right away if the urine test is positive for ketones (acetone) or if you have any of these symptoms. Fast, heavy breathing and rapid pulse are more severe symptoms and you should have medical attention right away. Severe, sustained hyperglycemia may result in diabetic coma and death.

ADVERSE REACTIONS

A few people with diabetes develop red, swollen and itchy skin where the insulin has been injected. This is called a “local reaction” and it may occur if the injection is not properly made, if the skin is sensitive to the cleansing solution, or if you are allergic to the insulin being used. If you have a local reaction, tell your physician.

Generalized insulin allergy occurs rarely, but when it does it may cause a serious reaction, including skin rash over the body, shortness of breath, fast pulse, sweating, and a drop in blood pressure. If any of these symptoms develop, you should seek emergency medical care.

If severe allergic reactions to insulin have occurred (i.e., generalized rash, swelling or breathing difficulties) you should be skin-tested with each new insulin preparation before it is used.

IMPORTANT NOTES

1. A change in the type, strength, species or purity of insulin could require a dosage adjustment. Any change in insulin should be made under medical supervision.
2. To avoid possible transmission of disease, PenFill cartridge should not be shared.
3. Before use, check that the PenFill cartridge is intact (e.g. no cracks). Do not use if any damage is visible, or if the part of the rubber piston that you see is wider than the white bar code band.
4. You may have learned how to test your urine or your blood for glucose. It is important to do these tests regularly and to record the results for review with your physician or nurse educator.
5. If you have an acute illness, especially with vomiting or fever, continue taking your insulin. If possible, stay on your regular diet. If you have trouble eating, drink fruit juices, regular soft drinks, or clear soups; if you can, eat small amounts of bland foods. Test your urine for glucose and ketones and, if possible, test your blood glucose. Note the results and contact your physician for possible insulin dose adjustment. If you have severe and prolonged vomiting, seek emergency medical care.
6. You should always carry identification which states that you have diabetes.
7. Always ask your physician or pharmacist before taking any drug.
8. Do not try to refill a PenFill cartridge.

Always consult your physician if you have any questions about your condition or the use of insulin.

Helpful information for people with diabetes is published by the American Diabetes Association, 1660 Duke Street, Alexandria, VA 22314

Date of issue: November 18, 2005

Protected by U.S. Patent No. 6,126,646 and No. 5,693,027 and Des. 347,894 and other U.S. Patents Pending, recommended for use with Novo Nordisk 3 mL PenFill cartridge compatible insulin delivery devices, with or without a NovoPen 3 PenMate, and Novo Nordisk pen needles.

© 2004/2005 Novo Nordisk Inc.

Novo Nordisk® , Novolin®, PenFill®, NovoPen®, PenMate®, NovoFine® and Lente® are registered trademarks owned by Novo Nordisk A/S.

Novo Nordisk Inc.

Princeton, NJ 08540

Call 1-800-727-6500 for additional information

www.novonordisk-us.com

Manufactured by

Novo Nordisk A/S

DK-2880 Bagsvaerd, Denmark

Patient Instructions for Use

Novolin 70/30® InnoLet®

Novolin® 70/30 InnoLet® directions for use

Novolin® 70/30 InnoLet® is a disposable dial-a-dose insulin delivery system able to deliver 1-50 units in increments of 1 unit. Novolin® 70/30 InnoLet® is designed and recommended for use with NovoFine® single-use needles. Novolin® 70/30 InnoLet® is not recommended for the blind or severely visually impaired patients without the assistance of a sighted individual trained in the proper use of this product.

Please read these instructions completely before using this device.

1. Preparing the Novolin® 70/30 InnoLet®:

Pull off the device cap.

1A. Turn the Novolin® 70/30 InnoLet® up and down between positions A and B so the glass ball is moved from one end of the insulin reservoir to the other. Do this at least 10 times, until the liquid appears uniformly white and cloudy.

To ensure even mixing of the remaining insulin there must be at least 12 units of insulin left in the reservoir. If there are less than 12 units left, do not use the Novolin® 70/30 InnoLet®.

Wipe rubber stopper with an alcohol swab.

1B. Remove the protective tab from the disposable needle and screw the needle onto the Novolin® 70/30 InnoLet®. Never place a disposable needle on your Novolin® 70/30 InnoLet® until you are ready to give an injection. Remove the needle immediately after use. If the needle is not removed, some liquid may be expelled from the Novolin® 70/30 InnoLet® causing a change in insulin concentration (strength).

1C. Giving the air shot prior to each injection:

Small amounts of air may collect in the needle and insulin reservoir during normal use. To avoid the injection of air and ensure proper dosing, dial 2 units by turning the dose selector clockwise. Hold the Novolin® 70/30 InnoLet® with the needle up and tap the Novolin® 70/30 InnoLet® gently with your finger so any air bubbles collect in the top of the reservoir. Remove both the plastic outer and inner needle caps.

With the needle pointing up, press the push button as far as it will go and the dose selector returns to zero. See if a drop of insulin appears at the needle tip (see fig. 1C). If not, repeat the procedure until insulin appears.

Before the first use of Novolin® 70/30 InnoLet® you may need to perform up to 6 air shots to get a drop of insulin at the needle tip. If you need to make more than 6 air shots, do not use, and return the product to Novo Nordisk. A small air bubble may remain but it will not be injected because the operating mechanism prevents the reservoir from being completely emptied.

2. Setting the dose

Always check that the push button is fully depressed and the dose selector is set to zero. Hold the Novolin® 70/30 InnoLet® in front of you and dial the dose selector clockwise to set the required dose. Do not put your hand over the push button when dialing the dose. If the button is not allowed to rise freely, insulin will be pushed out of the needle. When setting your dose, you will hear a click for every single unit dialed. Do not rely on this clicking sound as a means of determining your dose. If you have set a wrong dose, simply dial the dose selector forward or backwards until the right number of units has been set.

50 units is the maximum dose.

3. Giving the injection

Use the injection technique recommended by your doctor. Check that you have set the proper dose and depress the push button as far as it will go. Make sure not to block the dose selector while injecting as the dose selector must be allowed to return to zero when you press the push button. When depressing the push button you may hear a clicking sound. Do not rely on this clicking sound as a means of confirming delivery of your dose.

After making the injection, unscrew the needle and discard appropriately. Replace the device cap.

Health care professionals, relatives, and other care-givers should follow general precautionary measures for removal and disposal of needles to eliminate the risk of unintended needle penetration.

For additional information see Giving the injection on the reverse side of this insert.

Subsequent injections

Always check that the push button is fully depressed before using the Novolin® 70/30 InnoLet® again. If not, turn the dose selector until the push button is completely down. Then proceed as stated under steps 1-3. The numbers on the insulin reservoir can be used to estimate the amount of insulin left in the Novolin® 70/30 InnoLet®. These numbers are not used for measuring the insulin dose.

You cannot set a dose greater than the number of units remaining in the reservoir.

4. Function check

If you think that your Novolin® 70/30 InnoLet® is not working properly, follow this procedure:

a. Screw on a new NovoFine needle.

b. Perform air shot as described in section 1C.

c. Put the outer needle cap onto the needle.

d. Dispense 20 units into the needle cap.

The insulin will fill the lower part of the cap (as shown in fig. 4).

If the Novolin® 70/30 InnoLet® has released too much or too little insulin, repeat the test. If it happens again, contact Novo Nordisk and do not use your Novolin® 70/30 InnoLet®.

5. Important notes

a. If you need to perform more than 6 air shots before the first use of Novolin® 70/30 InnoLet® to get a drop of insulin at the needle tip, do not use.

b. Remember to perform an air shot before each injection (see fig. 1C).

c. Care should be taken not to drop the Novolin® 70/30 InnoLet® or subject it to impact.

d. Remember to keep the Novolin® 70/30 InnoLet® that you are currently using with you; don’t leave it in a car or other location where extremes of temperature can occur.

e. Novolin® 70/30 InnoLet® is designed and recommended for use with NovoFine disposable needles.

f. Never place a disposable needle on the Novolin® 70/30 InnoLet® until you are ready to use it. Remove the needle immediately after use.

g. Discard the used Novolin® 70/30 InnoLet® carefully, without the needle attached.

h. Always carry a spare Novolin® 70/30 InnoLet® with you in case your Novolin® 70/30 InnoLet® is damaged or lost.

i. Novo Nordisk cannot be held responsible for adverse reactions occurring as a consequence of using the insulin delivery system with products that are not recommended by Novo Nordisk.

KEEP OUT OF REACH OF CHILDREN

j. Keep Novolin® 70/30 InnoLet® out of the reach of children.

© 2002/2008 Novo Nordisk A/S

Call 800-727-6500 for additional information.

Novo Nordisk Inc.

Princeton, NJ 08540

www.novonordisk-us.com

Manufactured by

Novo Nordisk A/S

DK-2880 Bagsvaerd, Denmark

Novo Nordisk®, Novolin®, Lente®, NovoFine® and InnoLet® are trademarks owned by Novo Nordisk A/S

U.S. Patents Nos. 5,947,934, 6,074,372, 6,110,149, 6,302,869, 6,524,280, 6,379,339, 6,582,404, and other U.S. patents pending.

Principal Display Panel - 10 mL Vial

Novolin® 70/30 10 mL Vial

70% NPH, Human Insulin Isophane Suspension and

30% Regular, Human Insulin Injection

(recombinant DNA origin)

NDC 54868-3474-0

10 mL

Use with U-100 insulin syringes only

Shake carefully before use

Keep in cold place

Avoid freezing

Additional barcode labeling by:
Physicians Total Care, Inc.
Tulsa, Oklahoma 74146